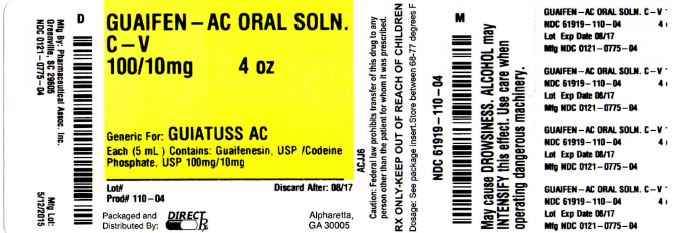 DRUG LABEL: GUAIFENESIN AND CODEINE PHOSPHATE
NDC: 61919-110 | Form: SOLUTION
Manufacturer: DirectRX
Category: otc | Type: HUMAN OTC DRUG LABEL
Date: 20151026
DEA Schedule: CV

ACTIVE INGREDIENTS: Guaifenesin 100 mg/5 mL; Codeine Phosphate 10 mg/5 mL
INACTIVE INGREDIENTS: edetate disodium; FD&C Blue No. 1; FD&C Red No. 40; FD&C Yellow No. 6; menthol; propylene glycol; sodium benzoate; sodium citrate; sorbitol

GUAIFENESIN AND CODEINE PHOSPHATE

DESCRIPTION SECTION

- Each 5 mL (1 teaspoonful) contains Guaifenesin, USP 100 mg and Codeine Phosphate, USP 10 mg.
  Inactive Ingredients: Citric acid, edetate disodium, FD&C Blue No. 1, FD&C Red No. 40, FD&C Yellow No. 6, flavor, glycerin, menthol, propylene glycol, purified water, sodium benzoate, sodium citrate, sodium saccharin, and sorbitol.
  Sodium Content: 5 mg/5 mL
  Under federal law, Guaifenesin and Codeine Phosphate Oral Solution USP is available without a prescription. Certain state laws may differ.

CONTRAINDICATIONS SECTION

Hypersensitivity to any of the ingredients

WARNINGS SECTION

- A persistent cough may be a sign of a serious condition. If cough persists for more than 1 week, tends to recur, or is accompanied by fever, rash or persistent headache, consult a physician. Do not take this product for persistent or chronic cough such as occurs with smoking, asthma, chronic bronchitis, emphysema, or if cough is accompanied by excessive phlegm (mucus) unless directed by a physician. Adults and children who have a chronic pulmonary disease or shortness of breath, or children who are taking other drugs, should not take this product unless directed by a physician. May cause or aggravate constipation. As with any drug, if you are pregnant or nursing a baby, seek the advice of a health professional before using this product.
  KEEP THIS AND ALL DRUGS OUT OF THE REACH OF CHILDREN. In case of accidental overdose, seek professional assistance or contact a Poison Control Center immediately.
  Professional Note: Guaifenesin has been shown to produce a color interference with certain clinical laboratory determinations of 5-hydroxyindoleacetic acid (5-HIAA) and vanillylmandelic acid (VMA).

DRUG INTERACTIONS SECTION

Caution should be used when taking this product with sedatives, tranquilizers and drugs used for depression, especially monoamine oxidase inhibitors (MAOIs). These combinations may cause greater sedation (drowsiness) than is caused by the products used alone. (See WARNINGS

DOSAGE & ADMINISTRATION SECTION

Take orally as stated below or use as directed by a physician. Adults and children 12 years of age and over: 10 mL (2 teaspoonfuls) every 4 hours, not to exceed 12 teaspoonfuls in a 24-hour period; Children 6 to under 12 years: 5 mL (1 teaspoonful) every 4 hours, not to exceed 6 teaspoonfuls in a 24-hour period; Children under 6 years: consult a physician. A special measuring device should be used to give an accurate dose of this product to children under 6 years of age. Giving a higher dose than recommended by a physician could result in serious side effects for a child. Use of codeine-containing preparations is not recommended for children under 2 years of age. Do not exceed recommended dosage.

STORAGE AND HANDLING SECTION

STORAGEKeep tightly closed. Store at controlled room temperature, 20°-25°C (68°-77°F). [See USP] Protect from light.

OTC - ACTIVE INGREDIENT SECTION

Each 5 mL (1 teaspoonful) contains Guaifenesin, USP 100 mg and Codeine Phosphate, USP 10 mg.

OTC - PURPOSE SECTION

Temporarily controls cough due to minor throat and bronchial irritation as may occur with the common cold or inhaled irritants. Helps loosen phlegm (mucus) and thin bronchial secretions to make coughs more productive.

OTC - KEEP OUT OF REACH OF CHILDREN SECTION

KEEP OUT OF REACH OF CHILDREN

INDICATIONS & USAGE SECTION

INDICATIONS

Temporarily controls cough due to minor throat and bronchial irritation as may occur with the common cold or inhaled irritants. Helps loosen phlegm (mucus) and thin bronchial secretions to make coughs more productive.

INACTIVE INGREDIENT SECTION

Citric acid, edetate disodium, FD&C Blue No. 1, FD&C Red No. 40, FD&C Yellow No. 6, flavor, glycerin, menthol, propylene glycol, purified water, sodium benzoate, sodium citrate, sodium saccharin, and sorbitol.